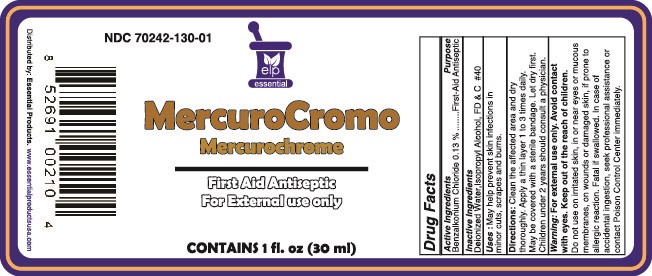 DRUG LABEL: Mercurochrome
NDC: 70242-130 | Form: SOLUTION
Manufacturer: Dannso Corp./d.b.a. Essential Products
Category: otc | Type: HUMAN OTC DRUG LABEL
Date: 20230101

ACTIVE INGREDIENTS: BENZALKONIUM CHLORIDE 0.13 g/1 mL
INACTIVE INGREDIENTS: WATER; ALCOHOL; FD&C RED NO. 40

Active Ingredients Purpose

Benzalkonium Chloride (0.13%) ................... First aid antiseptic

Use

May help prevent skin infection in

- minor cuts
- scrapes
- burns

Keep out of reach of children. If swallowed, get medical help or contact a Poison Control Center right away.

INDICATIONS AND USAGE

Mercurochrome

Mercury Free

First Aid Antiseptic

For External Use Only

Directions

- clean the affected area
- and dry thoroughly. Apply a thin layer 1 to 3 times daily.
- May be covered with a sterile bandage, let dry first.

Warnings For external use only

Avoid Contact with eyes.

When using this product

- do not use on irritated skin, in or near eyes or mocous membranes, on wounds or damaged skin, if prone to allergic reaction
- Fatal if swallowed.

Stop use and ask a doctor if condition persists or gets worse

INACTIVE INGREDIENT

Inactive Ingredients purified water, Isopropyl Alcohol, FD&C red # 40.